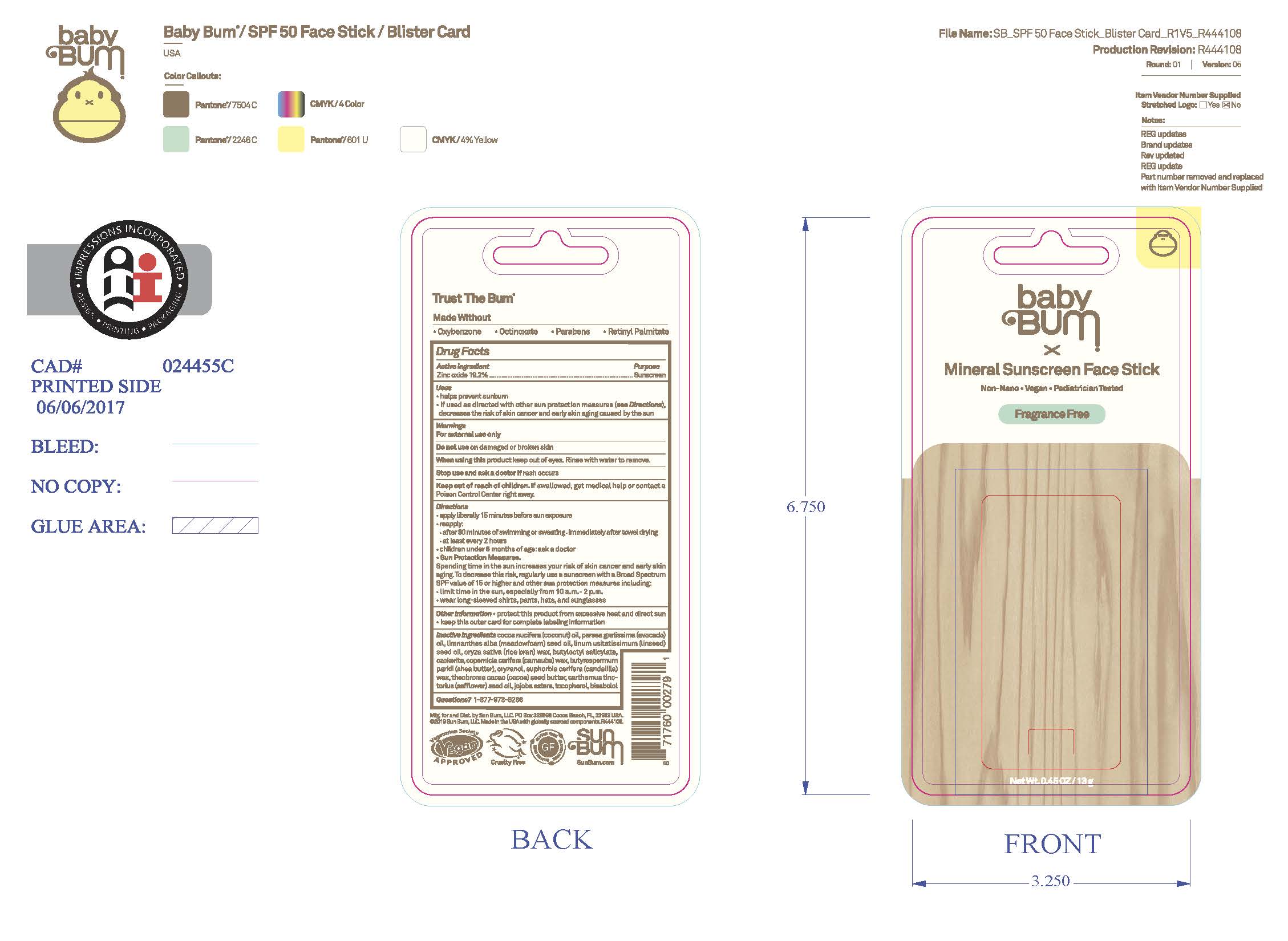 DRUG LABEL: Baby Bum Mineral 50 Mineral Sunscreen Face Stick
NDC: 69039-828 | Form: STICK
Manufacturer: Sun Bum, LLC
Category: otc | Type: HUMAN OTC DRUG LABEL
Date: 20250825

ACTIVE INGREDIENTS: ZINC OXIDE 192 mg/1 g
INACTIVE INGREDIENTS: CERESIN; BUTYLOCTYL SALICYLATE; ORYZANOL; CARTHAMUS TINCTORIUS (SAFFLOWER) SEED OIL; COCOS NUCIFERA (COCONUT) OIL; THEOBROMA CACAO (COCOA) SEED BUTTER; TOCOPHEROL; BISABOLOL; COPERNICIA CERIFERA (CARNAUBA) WAX; LINUM USITATISSIMUM (LINSEED) SEED OIL; BUTYROSPERMUM PARKII (SHEA) BUTTER; EUPHORBIA CERIFERA (CANDELILLA) WAX; HYDROLYZED JOJOBA ESTERS; LIMNANTHES ALBA (MEADOWFOAM) SEED OIL; RICE BRAN; PERSEA GRATISSIMA (AVOCADO) OIL

Baby Bum Mineral 50 Mineral Sunscreen Face Stick

Active Ingredients

Zinc Oxide 19.2%

Purpose

Sunscreen

Uses

• helps prevent sunburn • if used as directed with other sun protection measures, (see Directions) decreases the risk of skin cancer and early skin aging caused by the sun

Warnings

For external use only.

Do not use on damaged or broken skin

When using this product keep out of eyes. Rinse with water to remove.

Stop use and ask a doctor if rash occurs

Keep out of reach of children. If swallowed, get medical help or contact a Poison Control Center right away.

Warnings

Keep Out Of Reach Of Children

Directions

• apply liberally 15 minutes before sun exposure

• reapply: • after 80 minutes of swimming or sweating • immediately after towel drying • at least every 2 hours

• children under 6 months of age: ask a doctor

• Sun Protection Measures. Spending time in the sun increases your risk of skin cancer and early skin aging. To decrease this risk, regularly use a sunscreen with a Broad Spectrum SPF value of 15 or higher and other sun protection measures including:

• limit time in the sun, especially from 10 a.m.- 2 p.m.

• wear long-sleeved shirts, pants, hats and sunglasses

Directions

• apply liberally 15 minutes before sun exposure

Other Information

protect this product from excessive heat and direct sun

Inactive Ingredients

Cocos Nucifera (Coconut) Oil
Persea Gratissima (Avocado) Oil
Limnanthes Alba (Meadowfoam) Seed Oil
Linum Usitatissimum (Linseed) Seed Oil
Oryza Sativa (Rice Bran) Wax
Butyloctyl Salicylate
Ozokerite
Copernicia Cerifera (Carnauba) Wax
Butyrospermum Parkii (Shea Butter)
Oryzanol
Euphorbia Cerifera (Candelilla) Wax
Theobroma Cacao (Cocoa) Seed Butter
Carthamus Tinctorius (Safflower) Seed Oil
Jojoba Esters
Tocopherol
Bisabolol

Questions?

1-877-978-6286